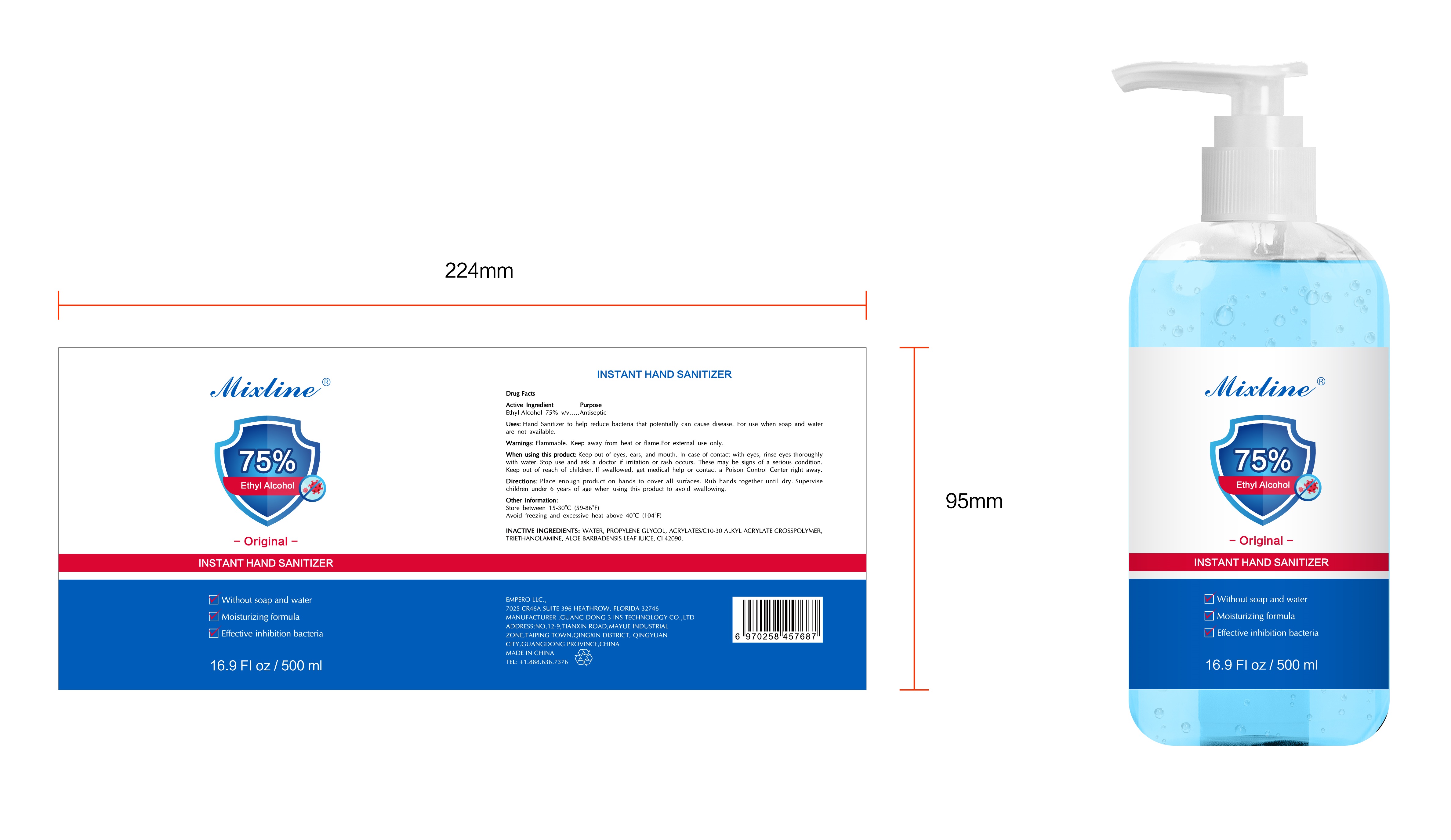 DRUG LABEL: Mixline 75% ethyl alcohol instant hand sanitizer
NDC: 75779-005 | Form: GEL
Manufacturer: GUANG DONG 3 INS TECHNOLOGY Co.,Ltd
Category: otc | Type: HUMAN OTC DRUG LABEL
Date: 20220822

ACTIVE INGREDIENTS: ALCOHOL 75 mL/100 mL
INACTIVE INGREDIENTS: PROPYLENE GLYCOL 1 g/100 mL; CARBOMER INTERPOLYMER TYPE A (ALLYL SUCROSE CROSSLINKED) 0.42 g/100 mL; WATER; TROLAMINE 0.42 g/100 mL; ALOE VERA LEAF 0.1 g/100 mL

Mixline 75% ethyl alcohol instant hand sanitizer

Active Ingredient

Ethyl Alcohol 75% v/v

Purpose

Antiseptic

Use

Hand Sanitizer to help reduce bacteria that potentially can cause disease. For use when soap and water are not available

Warnings

Flammable. Keep away from heat or flame For external use only
When using this product: Keep out of eyes, ears, and mouth. In case of contact with eyes, rinse eyes thoroughly with water Stop use and ask a doctor if irritation or rash occurs. These may be signs of a serious condition Keep out of reach of children. If swallowed, get medical help or contact a Poison Control Center right away

Directions

- Place enough product on hands to cover all surfaces. Rub hands together until dry.
- Supervise children under 6 years of age when using this product to avoid swallowing

Other information

store between 15-30 C (59-86 F)Avoid freezing and excessive heat above 40 C(104 F)

Inactive ingredients

WATER, PROPYLENE GLYCOL, ACRYLATES/C10-30 ALKYL ACRYLATE CROSSPOLYMERTRIETHANOLAMINE, ALOE BARBADENSIS LEAF JUICE, CI 42090.